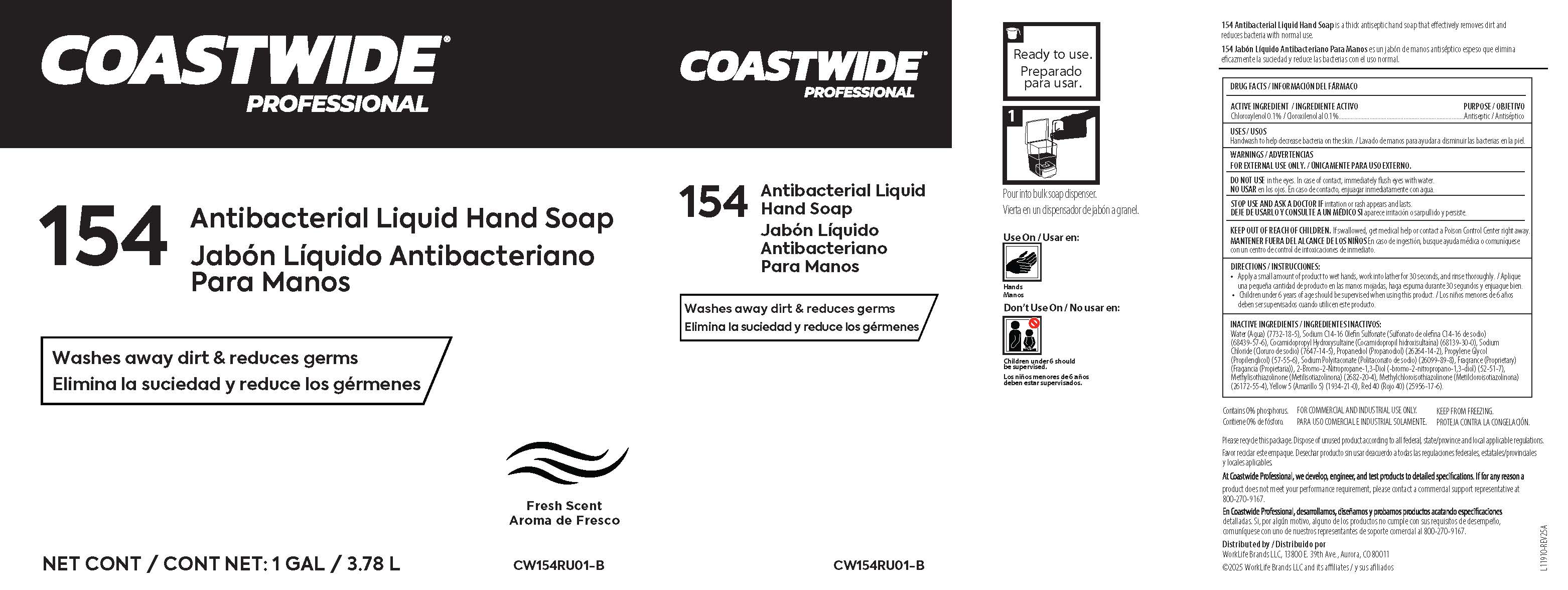 DRUG LABEL: 154 Antibacterial Liquid Hand
NDC: 80434-701 | Form: SOAP
Manufacturer: Worklife Brands, LLC
Category: otc | Type: HUMAN OTC DRUG LABEL
Date: 20250903

ACTIVE INGREDIENTS: CHLOROXYLENOL 1 g/1 L
INACTIVE INGREDIENTS: FD&C RED NO. 40; PROPANEDIOL; SODIUM POLYITACONATE (2800 MW, PHOSPHATE TERMINATED); BRONOPOL; WATER; FD&C YELLOW NO. 5; SODIUM C14-16 OLEFIN SULFONATE; SODIUM CHLORIDE; METHYLISOTHIAZOLINONE; PROPYLENE GLYCOL; METHYLCHLOROISOTHIAZOLINONE; COCAMIDOPROPYL HYDROXYSULTAINE

ACTIVE INGREDIENT / INGREDIENTE ACTIVO

Chloroxylenol 0.1% / Cloroxilenol al 0.1%

PURPOSE / OBJETIVO

Antiseptic / Antiséptico

USES / USOS

Handwash to help decrease bacteria on the skin. / Lavado de manos para ayudar a disminuir las bacterias en la piel.

WARNINGS / ADVERTENCIAS

FOR EXTERNAL USE ONLY. / ÚNICAMENTE PARA USO EXTERNO.

DO NOT USE in the eyes. In case of contact, immediately flush eyes with water.
NO USAR en los ojos. En caso de contacto, enjuagar inmediatamente con agua .

STOP USE AND ASK A DOCTOR IF irritation or rash appears and lasts.

DEJE DE USARLO Y CONSULTE A UN MÉDICO SI aparece irritación o sarpullido y persiste.

KEEP OUT OF REACH OF CHILDREN. If swallowed, get medical help or contact a Poison Control Center right away.

MANTENER FUERA DEL ALCANCE DE LOS NIÑOS. En caso de ingestión, busque ayuda médica o comuníquese
con un centro de control de intoxicaciones de inmediato.

DIRECTIONS / INSTRUCCIONES:

• Apply a small amount of product to wet hands, work into lather for 30 seconds, and rinse thoroughly. / Aplique
una pequeña cantidad de producto en las manos mojadas, haga espuma durante 30 segundos y enjuague bien.
• Children under 6 years of age should be supervised when using this product. / Los niños menores de 6 años
deben ser supervisados cuando utilicen este producto.

INACTIVE INGREDIENTS / INGREDIENTES INACTIVOS:

Water (Agua) (7732-18-5), Sodium C14-16 Olefin Sulfonate (Sulfonato de olefina C14-16 de sodio)
(68439-57-6), Cocamidopropyl Hydroxysultaine (Cocamidopropil hidroxisultaína) (68139-30-0), Sodium
Chloride (Cloruro de sodio) (7647-14-5), Propanediol (Propanodiol) (26264-14-2), Propylene Glycol
(Propilenglicol) (57-55-6), Sodium Polyitaconate (Politaconato de sodio) (26099-89-8), Fragrance (Proprietary)
(Fragancia (Propietaria)), 2-Bromo-2-Nitropropane-1,3-Diol (-bromo-2-nitropropano-1,3-diol) (52-51-7),
Methylisothiazolinone (Metilisotiazolinona) (2682-20-4), Methylchloroisothiazolinone (Metilcloroisotiazolinona)
(26172-55-4), Yellow 5 (Amarillo 5) (1934-21-0), Red 40 (Rojo 40) (25956-17-6).